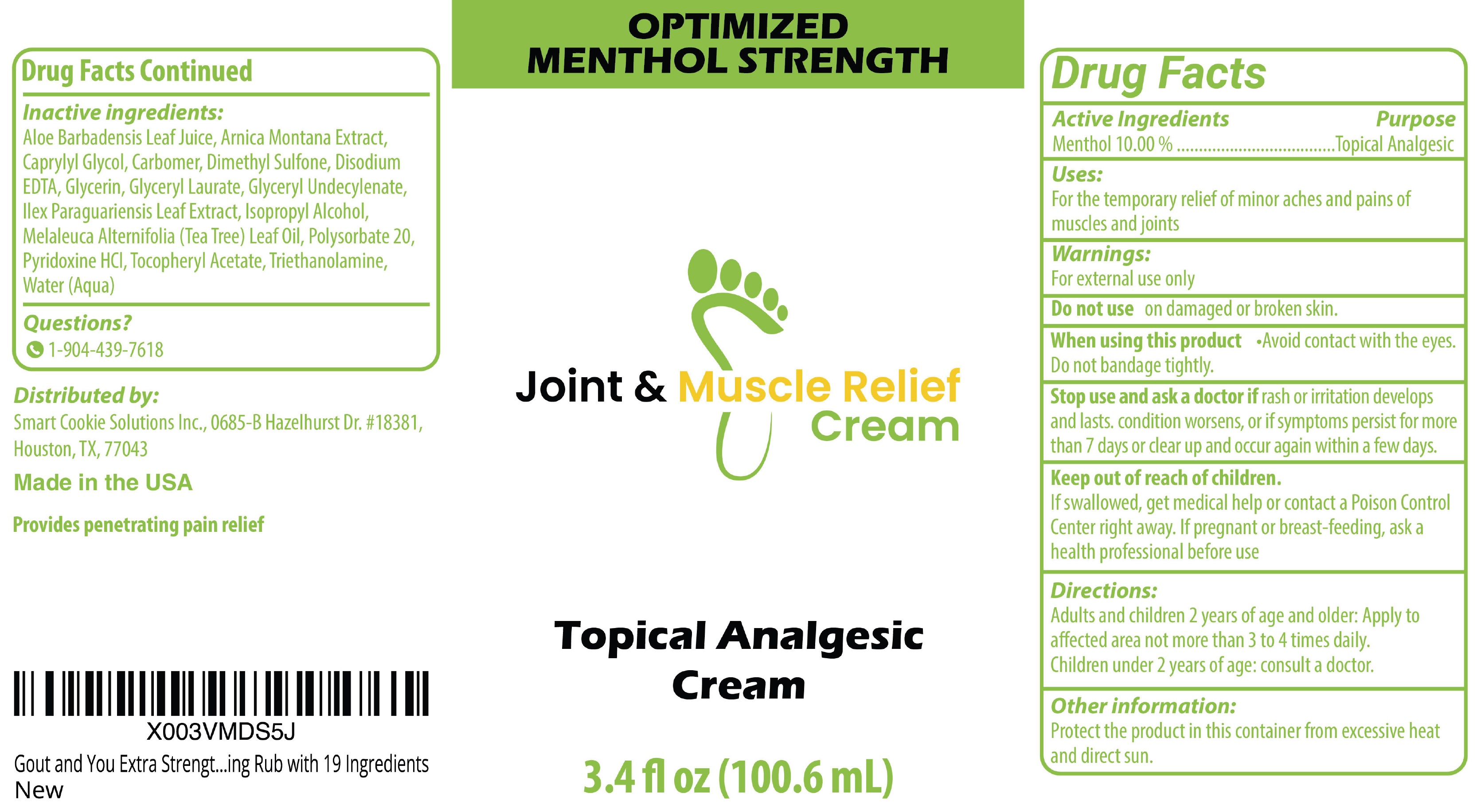 DRUG LABEL: Joint and Muscle Relief Topical Analgesic
NDC: 87282-988 | Form: CREAM
Manufacturer: Smart Cookie Solutions
Category: otc | Type: HUMAN OTC DRUG LABEL
Date: 20260128

ACTIVE INGREDIENTS: MENTHOL 100 mg/1 mL
INACTIVE INGREDIENTS: ALOE VERA LEAF; ARNICA MONTANA WHOLE; CAPRYLYL GLYCOL; CARBOMER HOMOPOLYMER, UNSPECIFIED TYPE; DIMETHYL SULFONE; EDETATE DISODIUM; GLYCERIN; GLYCERYL LAURATE; ILEX PARAGUARIENSIS LEAF; ISOPROPYL ALCOHOL; TEA TREE OIL; POLYSORBATE 20; PYRIDOXINE HYDROCHLORIDE; .ALPHA.-TOCOPHEROL ACETATE; TROLAMINE; WATER

Joint & Muscle Relief Topical Analgesic Cream

Active Ingredients

Menthol 10.00%

Purpose

Topical Analgesic

Uses:

For the temporary relief of minor aches and pains of muscles and joints

Warnings:

For external use only

Do not use

on damaged or broken skin.

When using this product

• Avoid contact with the eyes. Do not bandage tightly.

Stop use and ask a doctor if

rash or irritation develops and lasts. condition worsens, or if symptoms persist for more than 7 days or clear up and occur again with in a few days.

Keep out of reach of children.

If swallowed, get medical help or contact a Poison Control Center right away.

If pregnant or breast-feeding,

ask a health professional before use.

Directions:

Adults and children 2 years of age and older: Apply to affected area not more than 3 to 4 times daily. Children under 2 years of age: consult a doctor.

Other information:

Protect the product in this container from excessive heat and direct sun.

Inactive ingredients:

Aloe Barbadensis Leaf Juice,Arnica Montana Extract, Capryly lGlycol, Carbomer, Dimethyl Sulfone, Disodium EDTA, Glycerin, Glyceryl Laurate, Glyceryl Undecylenate, Ilex Paraguariensis Leaf Extract, Isopropyl Alcohol, Melaleuca Alternifolia (Tea Tree) Leaf Oil, Polysorbate 20, Pyridoxine HCI, Tocopheryl Acetate, Triethanolamine, Water (Aqua)

Questions?

1-904-439-7618